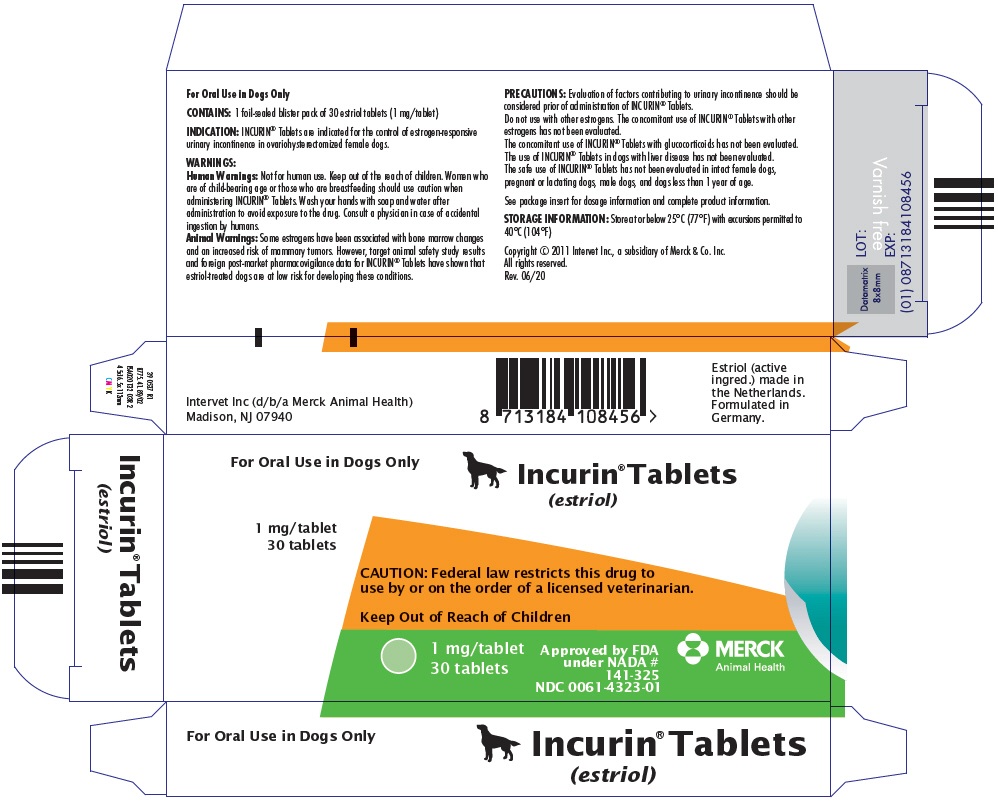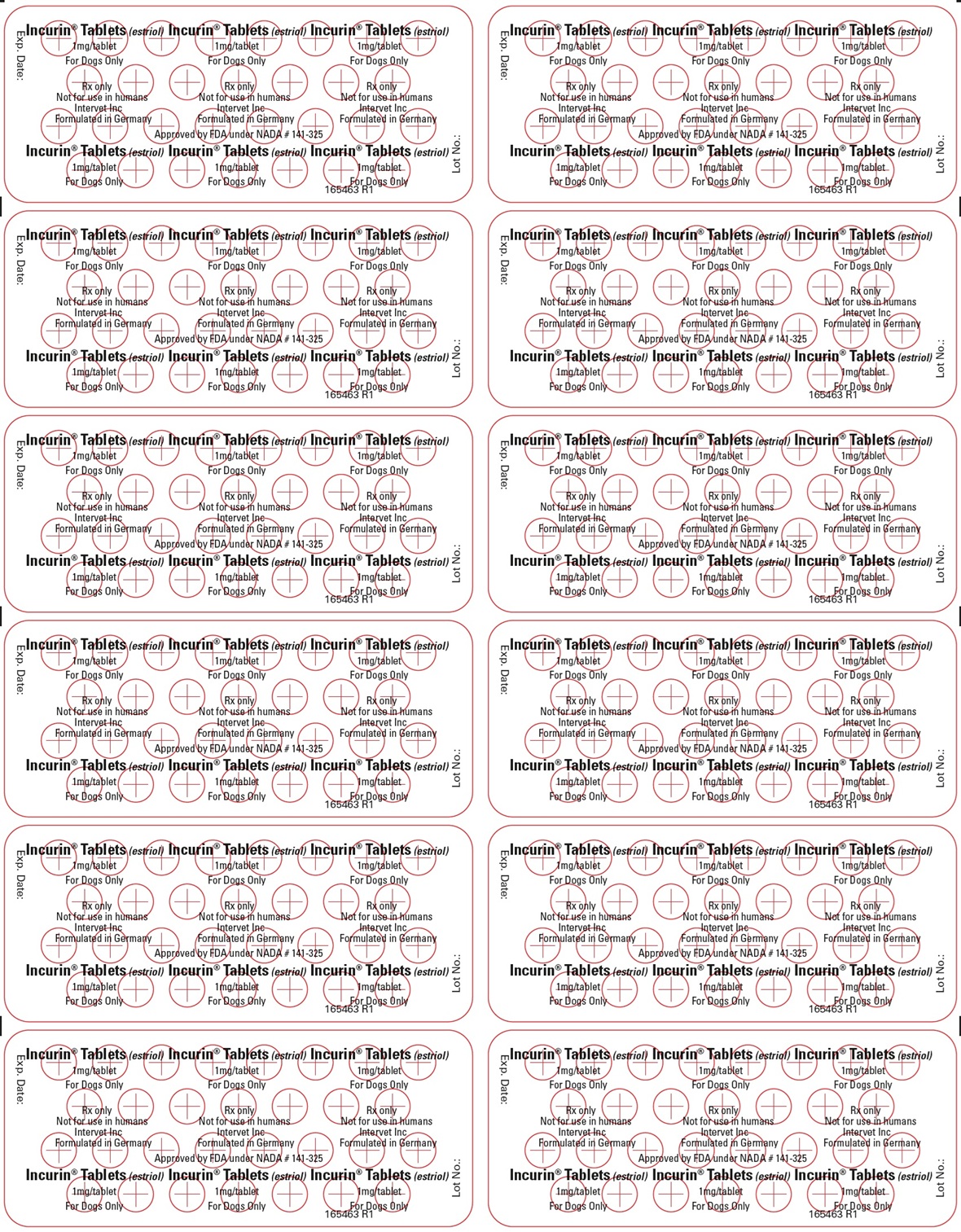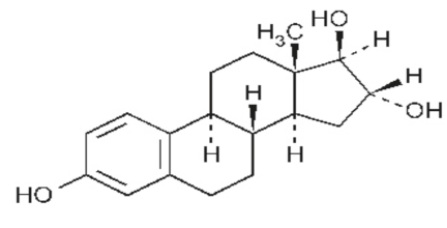 DRUG LABEL: Incurin
NDC: 0061-4323 | Form: TABLET
Manufacturer: Merck Sharp & Dohme Corp.
Category: animal | Type: PRESCRIPTION ANIMAL DRUG LABEL
Date: 20250304

ACTIVE INGREDIENTS: ESTRIOL 1 mg/1 1
INACTIVE INGREDIENTS: AMYLOPECTIN, UNSPECIFIED SOURCE; MAGNESIUM STEARATE; STARCH, POTATO; ANHYDROUS LACTOSE

INCURIN® Tablets
(estriol)

Approved by FDA under NADA # 141-325

INCURIN® Tablets

(estriol)

For Oral Use in Dogs Only

CAUTION: Federal law restricts this drug to use by or on the order of a licensed veterinarian.

DESCRIPTION:

INCURIN® (estriol) Tablets contain 1 mg of estriol per tablet.

USP Chemical Name: Estra-1,3,5(10)-triene-3,16,17-triol, (16α,17β)-.

USP Molecular Weight: 288.38

USP Solubility: Soluble in acetone, in chloroform, in dioxane, in ether, and in vegetable oils; sparingly soluble in alcohol; insoluble in water.

INDICATION:

INCURIN® Tablets are indicated for the control of estrogen-responsive urinary incontinence in ovariohysterectomized female dogs.

DOSAGE AND ADMINISTRATION:

The dose of INCURIN® Tablets is not dependent upon body weight. All dogs should receive an initial dose of 2 mg INCURIN® Tablets (2 tablets) orally once per day for a minimum of 14 days. After urinary incontinence is controlled, the lowest effective daily dose of INCURIN® Tablets should be determined by decreasing the dose in a step-wise manner from 2 mg once daily (2 tablets) to 1 mg once daily (1 tablet), then 0.5 mg once daily (1/2 tablet) depending upon the response of the individual dog. There should be a minimum of 7 days between each dose adjustment. After the lowest daily dose that controls urinary incontinence is identified, the dose may be decreased further by administering once every two days. Dogs should not receive more than 2 mg INCURIN® Tablets per day (2 tablets). If the dog does not respond to 2 mg of INCURIN® Tablets per day, the diagnosis should be re-assessed.

WARNINGS:

Human Warnings:

Not for human use. Keep out of the reach of children. Women who are of child-bearing age or those who are breastfeeding should use caution when administering INCURIN® Tablets. Wash your hands with soap and water after administration to avoid exposure to the drug. Consult a physician in case of accidental ingestion by humans.

Animal Warnings:

Some estrogens have been associated with bone marrow changes and an increased risk of mammary tumors. However, target animal safety study results and foreign post-market pharmacovigilance data for INCURIN® Tablets have shown that estriol-treated dogs are at low risk for developing these conditions.

PRECAUTIONS:

Evaluation of factors contributing to urinary incontinence should be considered prior of administration of INCURIN® Tablets.

Do not use with other estrogens. The concomitant use of INCURIN® Tablets with other estrogens has not been evaluated.

The concomitant use of INCURIN® Tablets with glucocorticoids has not been evaluated.

The use of INCURIN® Tablets in dogs with liver disease has not been evaluated.

The safe use of INCURIN® Tablets has not been evaluated in intact female dogs, pregnant or lactating dogs, male dogs, and dogs less than 1 year of age.

ADVERSE REACTIONS:

In the initial phase of a placebo-controlled field study conducted to determine effectiveness, 115 of 226 dogs were dosed with INCURIN® Tablets orally at 2 mg per day for 14 days. Adverse reactions during the first study phase included primarily gastrointestinal and estrogenic effects, as summarized in Table 1.

Table 1: Reported adverse reactions during 14 days of treatment with either INCURIN® Tablets dosed at 2 mg per day or placebo
Adverse Reaction | INCURIN® Tablet Group % of dogs (n = 115) | Placebo Group % of dogs (n = 111)
Anorexia | 13.0% | 3.6%
Emesis | 9.6% | 6.3%
Polydipsia | 7.0% | 7.2%
Swollen vulva | 4.3% | 0.0%
Anxiety | 3.5% | 2.7%
Sexual attractiveness | 3.5% | 1.8%
Somnolence | 1.7% | 0.0%
Hypersalivation | 1.7% | 0.0%
Estrous behavior | 0.9% | 0.0%
Mammary hyperplasia | 0.9% | 0.0%

In the second phase of the field study, all dogs received treatment with INCURIN® Tablets from Day 14 to Day 42; the drug dose was adjusted up or down (not to exceed 2 mg per day) at weekly intervals depending on whether urinary incontinence was controlled. Table 2 summarizes reported adverse reactions in dogs treated with INCURIN® Tablets during the second study phase. Adverse reactions tended to lessen when dogs received lower drug doses. One dog that received 10 doses of estriol was removed due to suspected uterine stump pyometra. The relationship between this adverse reaction and INCURIN® Tablets could not be determined.

Table 2: Reported adverse reactions during the second study phase (days 14-42)
Adverse Reaction | INCURIN® Tablets Group % of dogs (n = 224)
Anorexia | 12.9%
Emesis | 7.6%
Licking vulva | 4.5%
Swollen vulva | 4.0%
Vulvovaginitis | 4.0%
Lethargy | 4.0%
Polydipsia | 3.6%
Aggression | 1.8%
Hyperactivity | 1.8%
Cystitis | 1.3%
Anxiety | 0.9%
Mammary hyperplasia | 0.9%
Somnolence | 0.9%
Estrous behavior | 0.9%
Sexual attractiveness | 0.4%
Alopecia (local) | 0.4%

Extended-use studies continued after the field studies involving more than 300 dogs. Additional adverse reactions to those seen in the field studies included hyperpigmentation and lichenification of the vulva. Also, 3 dogs receiving INCURIN® Tablets were euthanized due to aggressive behavior.

Foreign market experience: Foreign post-market pharmacovigilance data for INCURIN® Tablets were collected from the years 2000 through 2010 by Intervet, Inc. Approximately 20% of reported adverse events were for local or general alopecia. Vaginal hemorrhage, possible stump pyometra, an increase in epileptic seizures, and anemia, leukopenia, and thrombocytopenia were seen in 1 or more dogs. Other adverse events reported were similar to those seen during the US studies.

For technical assistance or to report suspected adverse reactions call Intervet at 1-800-224-5318. For a copy of the Material Safety Data Sheet (MSDS), call 1-800-770-8878.

CLINICAL PHARMACOLOGY:

Estriol is a natural estrogen. Estrogens increase the resting muscle tone of the urethra in females and can be used to treat female dogs with urinary incontinence due to estrogen depletion. Estriol is rapidly absorbed after oral administration. It has a high affinity for receptors in cells of the lower urogenital tract, but a short receptor occupancy time that limits the undesirable effects of endometrial proliferation, skeletal muscle growth, and bone marrow suppression associated with long-term estrogen-estrogen receptor binding.

As one of the three naturally occurring estrogens, estriol is a lipophilic compound that can passively diffuse through cell membranes and bind to estrogen receptors in the nucleus to regulate gene expression. After an oral dose of 2 mg/dog/day in fed female dogs, Tmax occurred between 0.5-2 hrs (average 0.8 hrs) with corresponding Cmax values of 220-1150 pg/mL (average 650 pg/mL). Entero-hepatic recirculation and drug reabsorption may cause a second concentration peak in plasma around 4-12 hrs after dosing. Its elimination T½ ranges from 8 to 12 hours based on a multiple oral dose study in 6 adult female dogs.

However, the apparent estriol recycling observed in most dogs produced multiple peaks that confound the accurate determination of T½. The effect of prandial state on oral estriol bioavailability has not been evaluated. Repeated oral administration may result in elevated estriol systemic exposure.

EFFECTIVENESS:

A multi-site, masked, placebo-controlled field study was conducted to evaluate the effectiveness of INCURIN® Tablets. Two hundred and twenty-six client-owned, ovariohysterectomized female dogs 1 year of age or older with at least 3 episodes of urinary incontinence each week were randomly allocated to receive either INCURIN® Tablets or placebo. Two hundred and six dogs (106 treated with INCURIN® Tablets and 100 treated with placebo) from 22 sites were evaluated for effectiveness. Each dog was dosed orally with either two 1 mg tablets of INCURIN® Tablets or two tablets of placebo once per day for 14 days. During treatment, owners recorded the frequency of urinary incontinence episodes daily, and investigators rated response to treatment weekly (continent/improved or no change/worse). Treatment success was based upon response to treatment and a targeted reduction in the frequency of urinary incontinence episodes at Day 14 compared to Day 0. The proportion of dogs achieving treatment success was statistically significantly greater (p = 0.0038) in the group treated with INCURIN® Tablets (66%) than in the placebo-treated group (37%) at Day 14.

A second phase of the study evaluated decreasing doses of INCURIN® Tablets to control urinary incontinence. After Day 14, all dogs (224) received 2 tablets of INCURIN® Tablets (2 mg) orally once per day. Starting at Day 21, investigators were permitted to adjust the dose of INCURIN® Tablets up or down (not to exceed 2 mg per day) at weekly intervals until Day 42 if urinary continence was controlled. Dose information and urinary incontinence scoring was available for 191 dogs at the end of the study; ninety four dogs were receiving 2 mg of INCURIN® Tablets per day, and the other 96 dogs had dose reductions below 2 mg per day. Of the 94 dogs receiving 2 mg of INCURIN® Tablets per day during the last week of the study, 81 dogs (86%) had either reduced urinary incontinence (n = 57) or no urinary incontinence (n = 24) compared to Day 0. Of the ninety-seven dogs with dose reductions below 2 mg per day, all dogs receiving 1 mg of INCURIN® Tablets once daily (n = 41), 1 mg every other day (n = 5), or 0.5 mg every other day (n = 24) had either reduced or no incontinence compared to Day 0. Twenty-five of 26 dogs receiving 0.5 mg once daily had reduced or no incontinence, and one dog dosed with 2 mg of INCURIN® Tablets every other day had reduced incontinence.

There were no clinically significant changes in hematology or serum chemistry during either phase of the study.

ANIMAL SAFETY:

In a 26-week safety study, 24 healthy, ovariohysterectomized female Beagle dogs approximately 1 year of age, weighing 7.3 to 10.5 kg, were randomly divided into 4 groups of 6 animals each. INCURIN® Tablets were administered orally at doses of 0 (placebo), 1× (2 mg), 3× (6 mg) and 5× (10 mg) the maximum proposed label dose of 2 mg per dog per day. Estrogenic effects such as swollen vulva, mammary hyperplasia, and vulvar discharge occurred frequently in all dogs that received INCURIN® Tablets and increased in a dose-dependent manner. On gross necropsy, all dogs treated with INCURIN® Tablets had enlarged vulvas except 1 dog that received 2 mg per day. Microscopically, the vulvas and vaginas of treated dogs had a proestrus-like appearance, with or without a lymphoplasmacytic infiltrate. In addition, approximately one-third of the dogs in each group treated with INCURIN® Tablets had lymphoplasmacytic infiltrate and urothelium hyperplasia of the renal pelvis. One dog treated with 10 mg per day had urinary bladder inflammation. Dogs that received 6 mg and 10 mg of INCURIN® Tablets per day had increased white blood cell counts, absolute neutrophil counts and platelet counts compared to dogs in the other 2 groups. There were no changes related to INCURIN® Tablet administration noted in the microscopic evaluation of bone marrow smears. The myeloid:erythroid (M:E) cell ratios were comparable between dogs that received 10 mg of INCURIN® Tablets per day and those treated with placebo.

STORAGE INFORMATION:

Store at or below 25°C (77°F) with excursions permitted to 40°C (104°F)

HOW SUPPLIED:

INCURIN® Tablets contain 1 mg of estriol in each tablet and are supplied in foil-sealed blister packs of 30 single-scored tablets. Two carton sizes containing either 30 tablets (one blister pack) or 90 tablets (three blister packs) are available.

Formulated in Germany
Rev. 06/20

INCURIN® Tablets is the property of Intervet International B.V. or affiliated companies or licensors and is protected by copyrights, trademark and other intellectual property laws.
Copyright © 2011
Intervet International B.V.
All rights reserved.

MERCK
Animal Health

375061 R1/8775.80.89/02